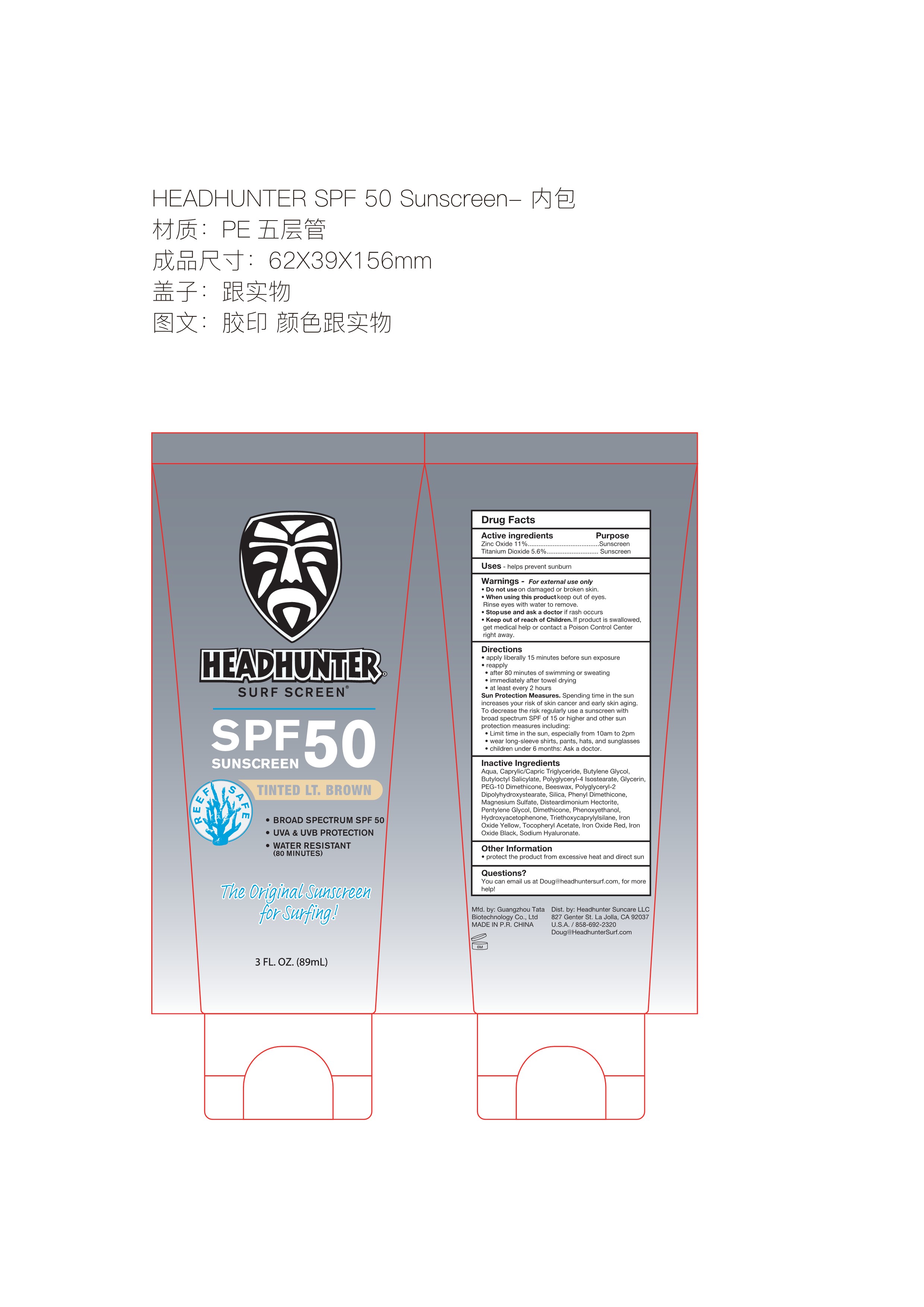 DRUG LABEL: HEADHUNTER SURF SCREEN SPF 50 SUNSCREEN
NDC: 84066-107 | Form: CREAM
Manufacturer: Guangzhou Tata Biotechnology Co., Ltd.
Category: otc | Type: HUMAN OTC DRUG LABEL
Date: 20251110

ACTIVE INGREDIENTS: TITANIUM DIOXIDE 5.6 mg/100 mL; ZINC OXIDE 11 mg/100 mL
INACTIVE INGREDIENTS: CI 77492; DIMETHICONE; TRIETHOXYCAPRYLYLSILANE; POLYGLYCERYL-4 ISOSTEARATE; BEESWAX; MAGNESIUM SULFATE; CI 77499; BUTYLOCTYL SALICYLATE; CAPRYLIC/CAPRIC TRIGLYCERIDE; BUTYLENE GLYCOL; DISTEARDIMONIUM HECTORITE; PENTYLENE GLYCOL; HYDROXYACETOPHENONE; GLYCERIN; AQUA; PEG-10 DIMETHICONE (600 CST); POLYGLYCERYL-2 DIPOLYHYDROXYSTEARATE; SILICA; DIPHENYL DIMETHICONE (400 CST); PHENOXYETHANOL; ALPHA-TOCOPHEROL ACETATE; CI 77491; SODIUM HYALURONATE

HEADHUNTER SURF SCREEN SPF 50 SUNSCREEN

ACTIVE INGREDIENT

Zinc Oxide 11%...........Sunscreen
Titanium Dioxide 5.6%........Sunscreen

PURPOSE

Sunscreen

INDICATIONS AND USAGE

helps prevent sunburn

WARNINGS

For external use only

Do not use on damaged or broken skin.

When using this product keep out of eyes.Rinse eyes with water to remove.

STOP USE

Stopuse and ask a doctor if rash occurs

Keep out of reach of Children.lf product is swallowed.get medical help or contact a Poison Control Centerright away.

Directions
apply liberally 15 minutes before sun exposure

reapply

after 80 minutes of swimming or sweating

immediately after towel drying

at least every 2 hoursSun Protection

Measures.Spending time in the sunincreases your risk of skin cancer and early skin agingTo decrease the risk regularly use a sunscreen withbroad spectrum SPF of 15 or higher and other sunprotection measures including:

Limit time in the sun, especially from 10am to 2pmwear long-sleeve shirts, pants, hats, and sunglasseschildren under 6 months: Ask a doctor.

INACTIVE INGREDIENT

Aqua, Caprylic/Capric Triglyceride, Butylene Glycol,Butyloctyl Salicylate, Polyglycery-4 lsostearate, Glycerin,PEG-10 Dimethicone,Beeswax, Polyglyceryl-2Dipolyhydroxystearate, Silica, Phenyl Dimethicone,Magnesium Sulfate, Disteardimonium Hectorite,Pentylene Glycol, Dimethicone, Phenoxyethanol.Hydroxyacetophenone, Triethoxycaprylylsilane, lronOxide Yellow, Tocopheryl Acetate, lron Oxide Red, lronOxide Black, Sodium Hyaluronate.

OTHER SAFETY INFORMATION

protect the product from excessive heat and direct sun

QUESTIONS

You can email us at Doug@headhuntersurf.com, for more help!